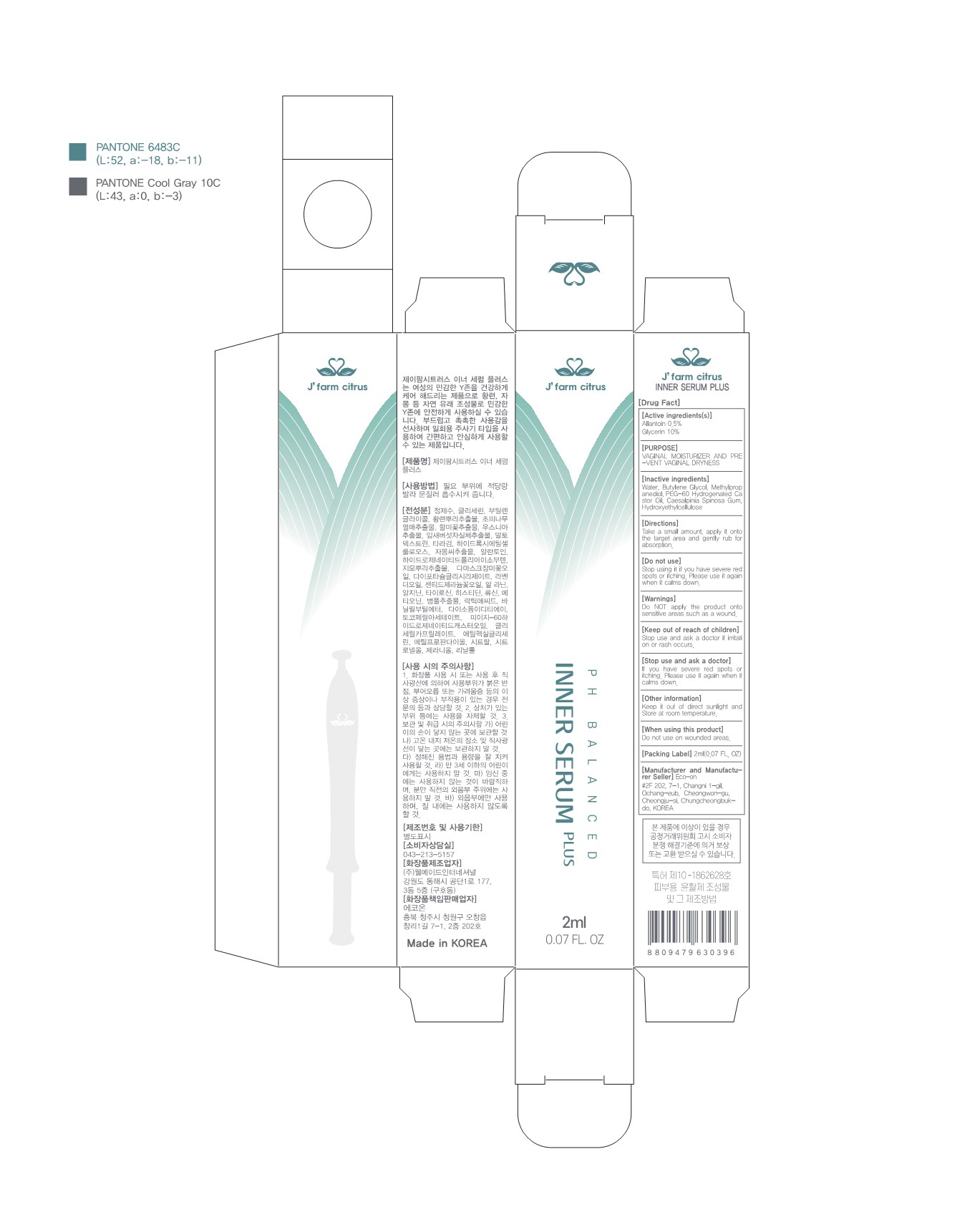 DRUG LABEL: J farm citrus Inner Serum plus
NDC: 80985-302 | Form: INJECTION
Manufacturer: Eco on
Category: otc | Type: HUMAN OTC DRUG LABEL
Date: 20230214

ACTIVE INGREDIENTS: GLYCERIN 10 mg/100 mL; ALLANTOIN 0.5 g/100 mL
INACTIVE INGREDIENTS: WATER; BUTYLENE GLYCOL; PEG-60 HYDROGENATED CASTOR OIL; HYDROXYETHYL CELLULOSE, UNSPECIFIED; CAESALPINIA SPINOSA RESIN; METHYLPROPANEDIOL

80985-302 J' farm citrus Inner Serum plus

Active Ingredient

Allantoin, Glycerin

Purpose

VAGINAL MOISTURIZER AND PREVENT VAGINAL DRYNESS

Inactive ingredients

Water, Butylene Glycol, Methylpropanediol, PEG-60 Hydrogenated Castor Oil, Caesalpinia Spinosa Gum, Hydroxyethylcellulose

Use

Take a small amount, apply it onto the target area and gently rub for absorption.

Directions

Keep it out of direct sunlight and Store at room temperature.

Do not use

Stop using it if you have severe red spots or itching. Please use it again when it calms down.

Warnings

Do NOT apply the product onto sensitive areas such as a wound.

Keep out of reach of children

Stop use and ask a doctor if irritation or rash occurs.

Stop use and ask a doctor

If you have severe red spots or itching. Please use it again when it calms down.

When using this product

Do not use on wounded areas.